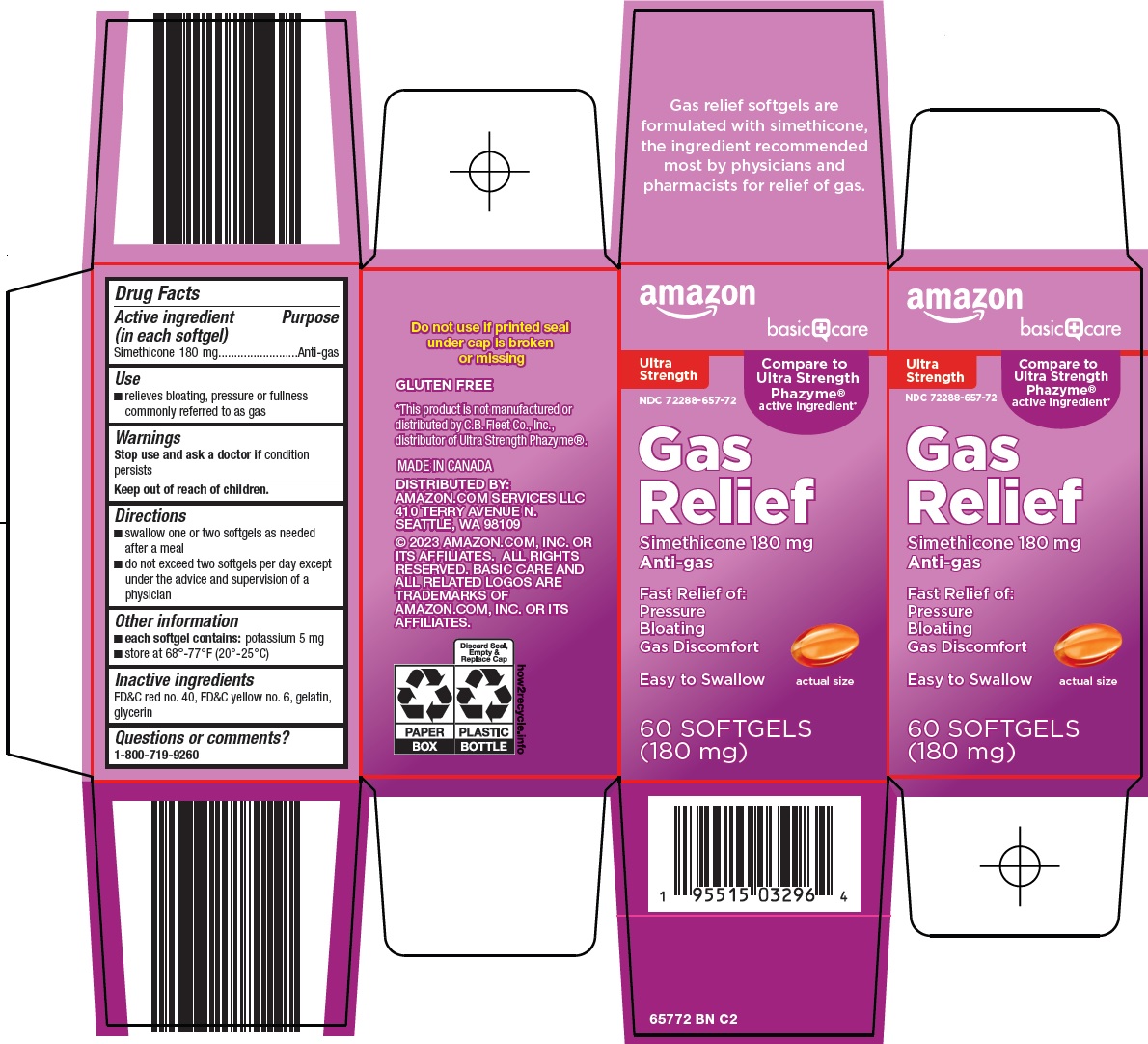 DRUG LABEL: basic care gas relief
NDC: 72288-657 | Form: CAPSULE, LIQUID FILLED
Manufacturer: Amazon.com Services LLC
Category: otc | Type: HUMAN OTC DRUG LABEL
Date: 20240914

ACTIVE INGREDIENTS: DIMETHICONE 180 mg/1 1
INACTIVE INGREDIENTS: SILICON DIOXIDE; FD&C RED NO. 40; FD&C YELLOW NO. 6; GELATIN, UNSPECIFIED; GLYCERIN

Amazon Gas Relief Drug Facts

Active ingredient (in each softgel)

Simethicone 180 mg

Purpose

Anti-gas

Use

1. relieves bloating, pressure or fullness commonly referred to as gas

Warnings

Stop use and ask a doctor if

condition persists

Directions

1. swallow one or two softgels as needed after a meal
2. do not exceed two softgels per day except under the advice and supervision of a physician

Other information

1. each softgel contains: potassium 5 mg
2. store at 68°-77°F (20°-25°C)

Inactive ingredients

FD&C red no. 40, FD&C yellow no. 6, gelatin, glycerin

Questions or comments?

1-800-719-9260

Principal Display Panel

amazon

basic care

Ultra Strength

Compare to Ultra Strength Phazyme® active ingredient

Gas Relief

Simethicone 180 mg

Anti-gas

Fast Relief of:

Pressure

Bloating

Gas Discomfort

Easy to Swallow

actual size

60 SOFTGELS (180 mg)